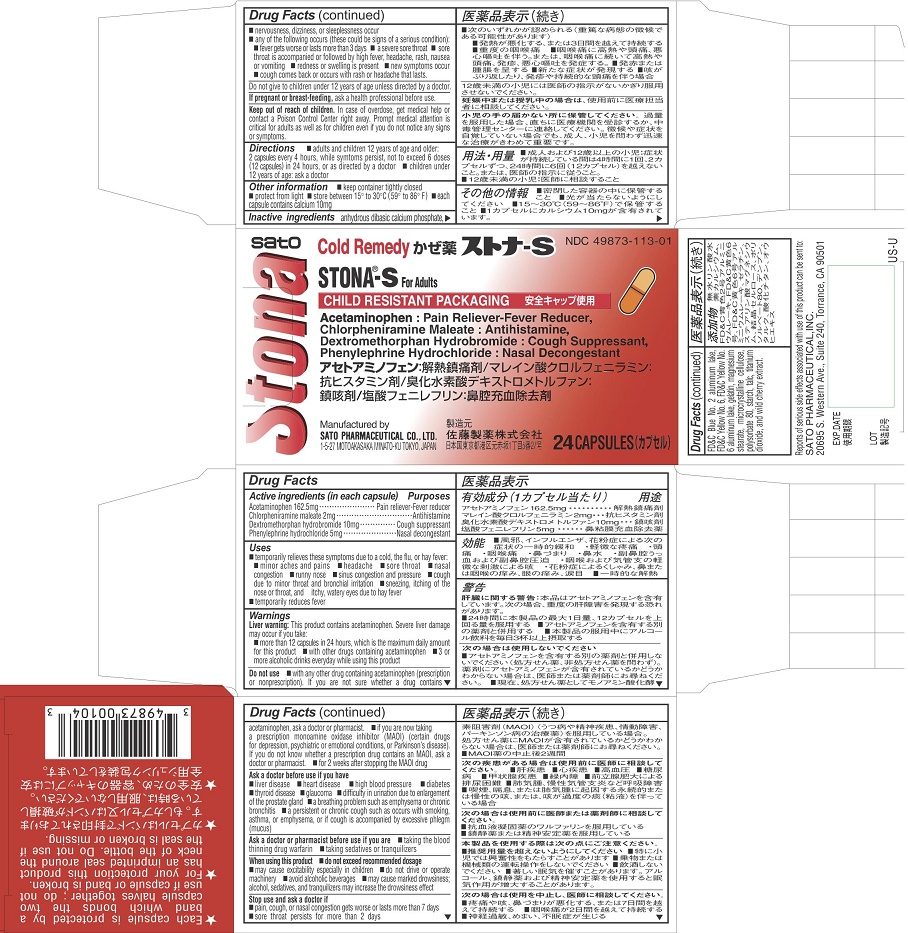 DRUG LABEL: Stona-S
NDC: 49873-113 | Form: CAPSULE
Manufacturer: Sato Pharmaceutical Co., Ltd.
Category: otc | Type: HUMAN OTC DRUG LABEL
Date: 20231204

ACTIVE INGREDIENTS: ACETAMINOPHEN 162.5 mg/1 1; CHLORPHENIRAMINE MALEATE 2 mg/1 1; DEXTROMETHORPHAN HYDROBROMIDE 10 mg/1 1; PHENYLEPHRINE HYDROCHLORIDE 5 mg/1 1
INACTIVE INGREDIENTS: CALCIUM PHOSPHATE, DIBASIC, ANHYDROUS; FD&C BLUE NO. 2; ALUMINUM OXIDE; FD&C YELLOW NO. 6; GELATIN; MAGNESIUM STEARATE; CELLULOSE, MICROCRYSTALLINE; POLYSORBATE 80; STARCH, CORN; TALC; TITANIUM DIOXIDE

Stona-S Capsules

Active ingredients (in each capsule)
Acetaminophen 162.5 mg
Chlorpheniramine maleate 2 mg
Dextromethorphan hydrobromide 10mg
Phenylephrine hydrochloride 5 mg

Purposes
Acetaminophen Pain reliever-fever reducer
Chlorpheniramine maleate Antihistamine
Dextromethorphan hydrobromide Cough suppressant
Phenylephrine hydrochloride Nasal decongestant

Uses
■temporarily relieves these symptoms due to a cold, the flu, or hay fever:
■minor aches and pains ■headache ■sore throat ■nasal congestion
■runny nose ■sinus congestion and pressure
■cough due to minor throat and bronchial irritation
■sneezing, itching of the nose or throat, and itchy, watery eyes due to hay fever
■temporarily reduces fever

Warnings
Liver warning: This product contains acetaminophen. Severe liver damage may occur if you take:
■more than 12 capsules in 24 hours, which is the maximum daily amount for this product
■with other drugs containing acetaminophen
■3 or more alcoholic drinks everyday while using this product

Do not use
■ with any other drug containing acetaminophen (prescription or nonprescription). If you
are not sure whether a drug contains acetaminophen, ask a doctor or pharmacist.
■ if you are now taking a prescription monoamine oxidase inhibitor (MAOI) (certain drugs for
depression, psychiatric or emotional conditions, or Parkinson’s disease). If you do not
know whether a prescription drug contains an MAOI, ask a doctor or pharmacist.
■ for 2 weeks after stopping the MAOI drug

Ask a doctor before use if you have
■ liver disease ■ heart disease ■ high blood pressure ■ diabetes
■ thyroid disease ■ glaucoma
■ difficulty in urination due to enlargement of the prostate gland
■ a breathing problem such as emphysema or chronic bronchitis
■ a persistent or chronic cough such as occurs with smoking, asthma, or emphysema, or if cough is accompanied by excessive phlegm (mucus)

Ask a doctor or pharmacist before use if you are
■taking the blood thinning drug warfarin
■taking sedatives or tranquilizers

When using this product
■do not exceed recommended dosage
■may cause excitability especially in children
■do not drive or operate machinery
■avoid alcoholic beverages
■may cause marked drowsiness; alcohol, sedatives, and tranquilizers may increase the
drowsiness effect

Stop use and ask a doctor if

- pain, cough, or nasal congestion gets worse or lasts more than 7 days
- sore throat persists for more than 2 days
- nervousness, dizziness, or sleeplessness occur
- any of the following occurs (these could be signs of a serious condition):
- fever gets worse or or lasts more than 3 days
- a severe sore throat
- sore throat is accompanied or followed by high fever, headache, rash, nausea or vomiting
- redness or swelling is present
- new symptoms occur
- cough comes back or occurs with rash or headache that lasts

PRECAUTIONS

Do not give to children under 12 years of age unless directed by a doctor.

PREGNANCY OR BREAST FEEDING

If pregnant or breast-feeding, ask a health professional before use.

Keep out of reach of children. In case of overdose, get medical help or contact a Poison
Control Center right away. Prompt medical attention is critical for adults as well as for
children even if you do not notice any signs or symptoms.

Directions
■adults and children 12 years of age and older: 2 capsules every 4 hours, while symptoms
persist, not to exceed 6 doses (12 capsules) in 24 hours, or as directed by a doctor
■children under 12 years of age: ask a doctor

Other information
■keep container tightly closed ■protect from light ■store between 15° to 30°C (59° to
86° F)
■each capsule contains calcium 10 mg

Inactive ingredients
dibasic calcium phosphate, FD and C Blue No. 2 Alminum lake, FD and C Yellow No. 6, FD and C
Yellow No. 6 Aluminum lake, gelatin, magnesium stearate, microcrystalline cellulose,
polysorbate 80, starch, talc, titanium dioxide, and wild cherry extract.